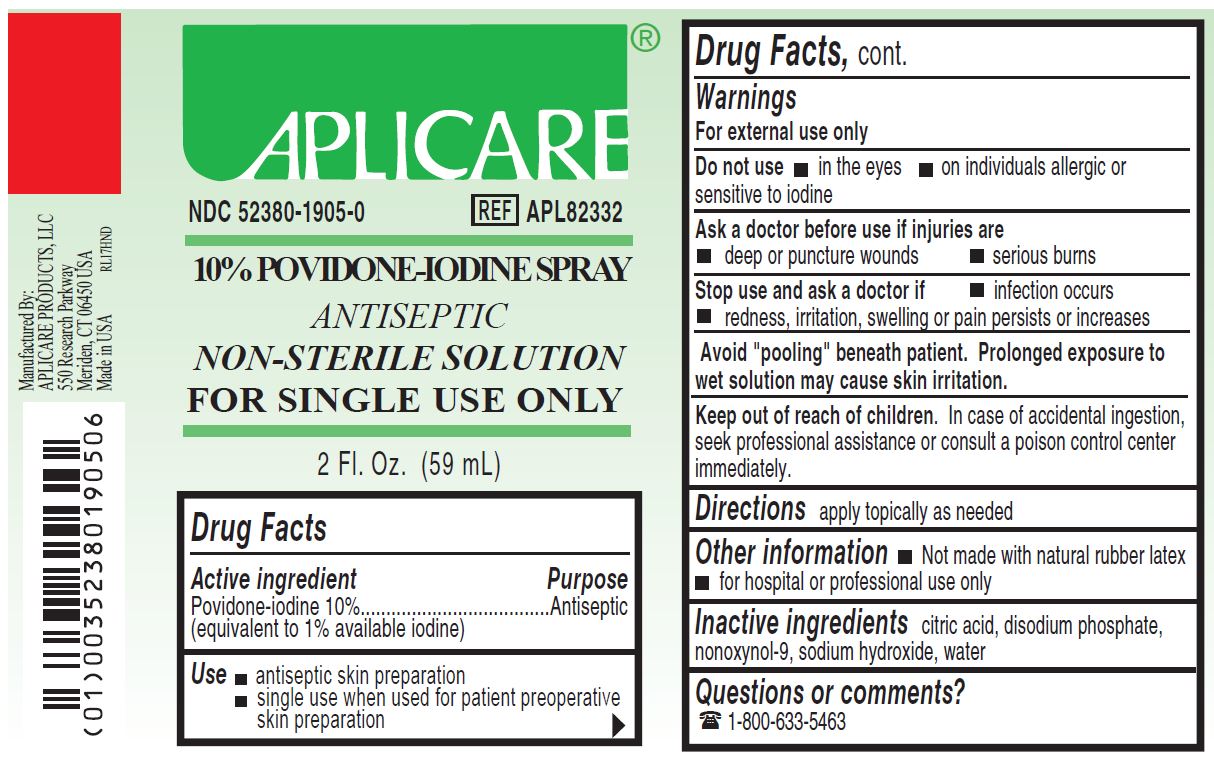 DRUG LABEL: Aplicare Povidone-Iodine
NDC: 52380-1905 | Form: SOLUTION
Manufacturer: Aplicare Products, LLC
Category: otc | Type: HUMAN OTC DRUG LABEL
Date: 20251218

ACTIVE INGREDIENTS: POVIDONE-IODINE 10 mg/1 mL
INACTIVE INGREDIENTS: CITRIC ACID MONOHYDRATE; SODIUM PHOSPHATE, DIBASIC; SODIUM HYDROXIDE; NONOXYNOL-9; WATER

1905 10% PVP-I Scrub, Non-Sterile

Active ingredient

Povidone-iodine USP 10%

Purpose

Antiseptic

Warnings

For external use only

Avoid "pooling" beneath patient. Prolonged exposure to wet solution may cause skin irritation.

Do not use

- in the eyes
- on individuals allergic or sensitive to iodine

Ask a doctor before use if injuries are

- deep or puncture wounds
- serious burns

Stop use and ask a doctor if

- infection occurs
- redness, irritation, swelling or pain persists or increases

Keep out of reach of children.

In case of accidental ingestion, seek professional assistance or consult a poison control center immediately.

Uses

- antiseptic skin preparation
- single use when used for patient preoperative skin preparation and/or preinjection indications.

Directions

apply locally as needed

Other information

- 1% titratable iodine
- not made with Natural Rubber Latex
- for hospital or professional use only

Inactive ingredients

• citric acid

• disodium phosphate

• nonoxynol-9

• sodium hydroxide

• water

Questions or comments?

1 800-633-5463

Monday - Friday

8:30 AM -5:00 PM EST

Manufacturing Information

Manufactured by:
Aplicare Products, LLC
550 Research Parkway, Meriden, CT 06450 USA

Made in USA with domestic and foreign materials
1-800-633-5463
REF: APL82332
RL17HND